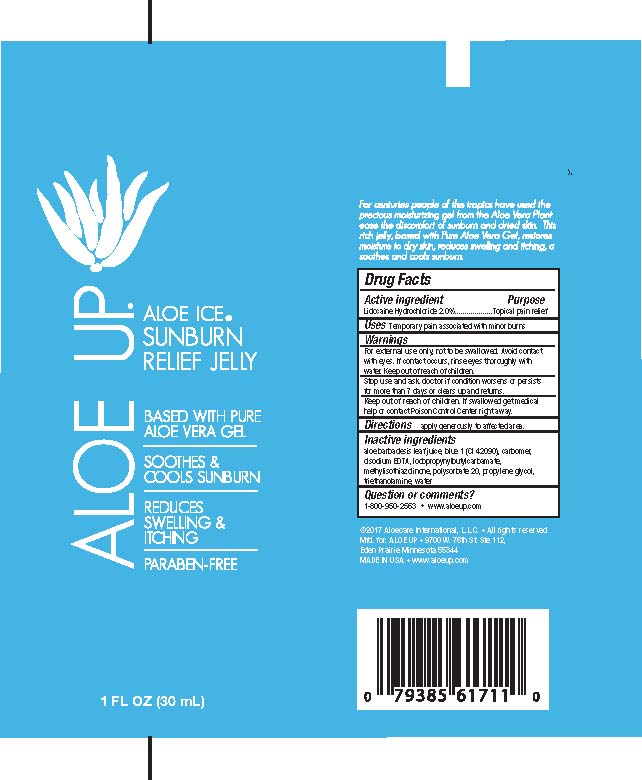 DRUG LABEL: ALOE ICE SUNBURN RELIEF
NDC: 61477-101 | Form: GEL
Manufacturer: Aloe Care International, LLC
Category: otc | Type: HUMAN OTC DRUG LABEL
Date: 20260128

ACTIVE INGREDIENTS: LIDOCAINE HYDROCHLORIDE 2 g/100 mL
INACTIVE INGREDIENTS: ALOE VERA WHOLE; FD&C BLUE NO. 1; CARBOMER 934; EDETATE DISODIUM; IODOPROPYNYL BUTYLCARBAMATE; METHYLISOTHIAZOLINONE; POLYSORBATE 20; PROPYLENE GLYCOL; TROLAMINE; WATER

ALOE UP - ALOE ICE SUNBURN RELIEF JELLY (61477-101)

ACTIVE INGREDIENTS

LIDOCAINE HYDROCHLORIDE 2%

PURPOSE

PAIN RELIEF

USES

TEMPORARY PAIN ASSOCIATED WITH MINOR BURNS

DIRECTIONS

APPLY GENEROUSLY TO AFFECTED AREA.

KEEP OUT OF REACH OF CHILDREN.

WARNINGS

FOR EXTERNAL USE ONLY, NOT TO BE SWALLOWED. AVOID CONTACT WITH EYES. IF CONTACT OCCURS, RINSE EYES THOROUGHLY WITH WATER.

STOP USE AND ASK A DOCTOR IF CONDITION WORSENS OR PERSISTS FOR MORE THAN 7 DAYS OR CLEARS UP AND RETURNS.

INACTIVE INGREDIENTS

Aloe Barbadensis Leaf Juice, Blue 1 (CI 42090), Carbomer, Disodium EDTA, Iodopropynyl Butylcarbamate, Methylisothiazolinone, Polysorbate 20, Propylene Glycol, Triethanolamine, Water

QUESTIONS OR COMMENTS?

1-800-950-2563 * WWW.ALOEUP.COM